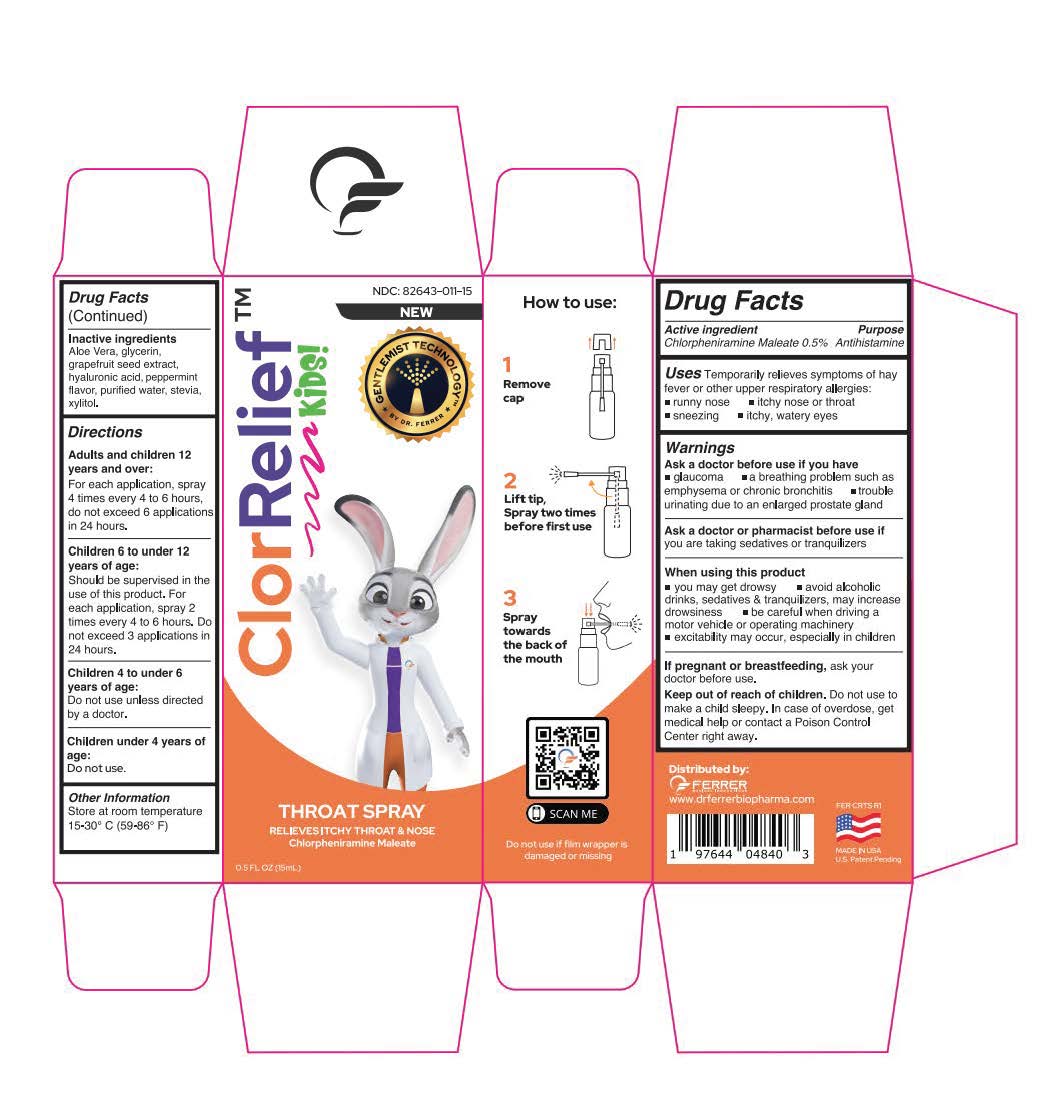 DRUG LABEL: ClorRelief KIDs
NDC: 82643-011 | Form: AEROSOL, SPRAY
Manufacturer: FERRER MEDICAL INNOVATIONS LLC
Category: otc | Type: HUMAN OTC DRUG LABEL
Date: 20230424

ACTIVE INGREDIENTS: CHLORPHENIRAMINE MALEATE 5 mg/1 mL
INACTIVE INGREDIENTS: XYLITOL; WATER; GLYCERIN; ALOE VERA WHOLE; PEPPERMINT; GRAPEFRUIT SEED OIL; HYALURONIC ACID; STEVIA LEAF

ClorRelief KIDs (Chlorpheniramine Maleate 0.5%) Antihistamine Oral Spray

Active ingredient

Chlorpheniramine Maleate 0.5%

Purpose

Antihistamine

Uses

Temporarily relieves symptoms of hay fever or other upper respiratory allergies:

- runny nose
- itchy nose or throat
- sneezing itchy, watery eyes

Warnings

Ask a doctor before use if you have

glaucoma a breathing problem such as emphysema or chronic bronchitis trouble urinating due to an enlarged prostate gland

Ask a doctor or pharmacist before use if

you are taking sedatives or tranquilizers

When using this product

- you may get drowsy
- avoid alcoholic drinks, sedatives & tranquilizers, may increase drowsiness
- be careful when driving a motor vehicle or operating machinery
- excitability may occur, especially in children

If pregnant or breastfeeding,

ask your doctor before use.

Keep out of reach of children

Do not use to make a child sleepy. In case of overdose, getmedical help or contact a Poison Control Center right away.

Inactive ingredients

Aloe Vera, glycerin, grapefruit seed extract, hyaluronic acid, peppermint flavor, purified water, stevia, xylitol.

Directions

Adults and children 12 years and over:

For each application, spray 4 times every 4 to 6 hours,

do not exceed 6 applications in 24 hours.

Children 6 to under 12 years of age:
Should be supervised in the use of this product. For each application, spray 2 times every 4 to 6 hours. Do not exceed 3 applications in 24 hours.

Children 4 to under 6 years of age:
Do not use unless directed by a doctor.

Children under 4 years of age:
Do not use.

Other Information

Store at room temperature 15-30° C (59-86° F)